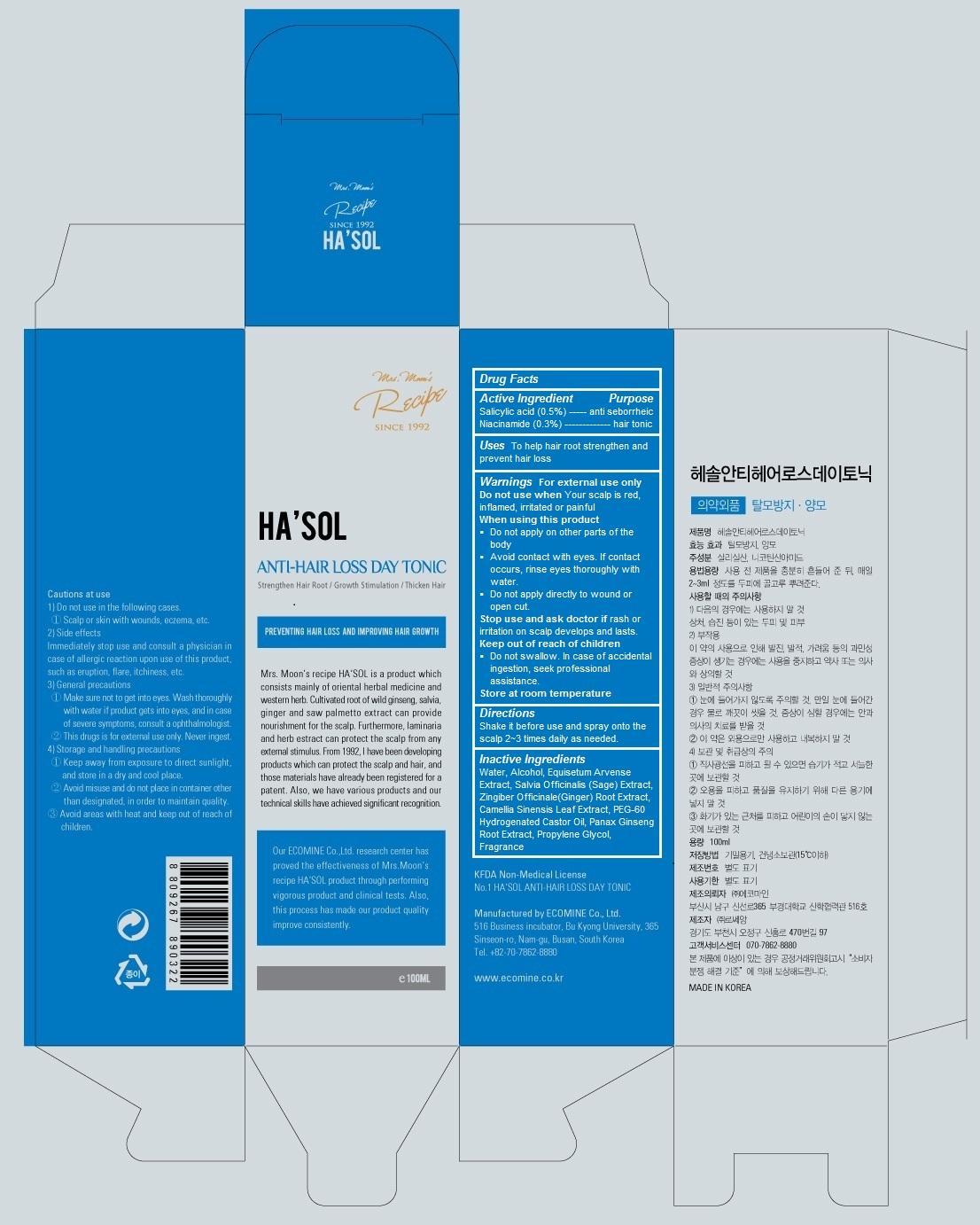 DRUG LABEL: Hasol Anti Hair loss day tonic
NDC: 51270-121 | Form: SPRAY
Manufacturer: Ecomine Co., Ltd.
Category: otc | Type: HUMAN OTC DRUG LABEL
Date: 20140725

ACTIVE INGREDIENTS: Salicylic Acid 0.5 1/100 mL; Niacinamide 0.3 1/100 mL
INACTIVE INGREDIENTS: Water; Alcohol; EQUISETUM ARVENSE WHOLE; SALVIA OFFICINALIS WHOLE; ZINGIBER OFFICINALE WHOLE; CAMELLIA SINENSIS WHOLE; PEG-60 HYDROGENATED CASTOR OIL; PANAX GINSENG ROOT OIL; PROPYLENE GLYCOL

HA'SOL Anti Hair loss day tonic